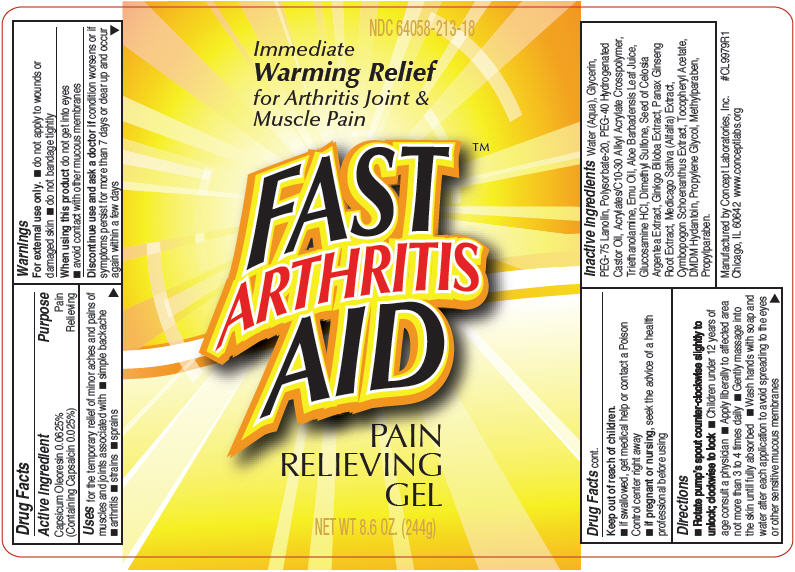 DRUG LABEL: Fast Arthritis Aid
NDC: 64058-213 | Form: GEL
Manufacturer: Concept Laboratories, Inc.
Category: otc | Type: HUMAN OTC DRUG LABEL
Date: 20150522

ACTIVE INGREDIENTS: Capsicum Oleoresin 0.061 g/244 g
INACTIVE INGREDIENTS: Water; Glycerin; PEG-75 LANOLIN; DIMETHYL SULFONE; ALOE VERA LEAF; ALFALFA LEAF; CYMBOPOGON SCHOENANTHUS LEAF; GLUCOSAMINE HYDROCHLORIDE; GINKGO; POLYSORBATE 20; EMU OIL; DMDM HYDANTOIN; PROPYLENE GLYCOL; METHYLPARABEN; PROPYLPARABEN; ASIAN GINSENG; .ALPHA.-TOCOPHEROL ACETATE; POLYOXYL 40 HYDROGENATED CASTOR OIL; TROLAMINE

FAST ARTHRITIS AID
Pain Relieving Gel

Drug Facts

Active ingredient

Capsicum Oleoresin 0.0625% (Containing Capsaicin 0.025%)

Purpose

Pain Relieving

Uses

for the temporary relief of minor aches and pains of muscles and joints associated with

- arthritis
- strains
- sprains

Warnings

For external use only.

- do not apply to wounds or damaged skin
- do not bandage tightly

When using this product do not get into eyes

- avoid contact with other mucous membranes

STOP USE

Discontinue use and ask a doctor if condition worsens or if symptoms persist for more than 7 days or clear up and occur again within a few days

Keep out of reach of children.

- if swallowed, get medical help or contact a Poison Control center right away

PREGNANCY OR BREAST FEEDING

- if pregnant or nursing, seek the advice of a health professional before using

Directions

- Rotate pump's spout counter-clockwise slightly to unlock; clockwise to lock
- Children under 12 years of age consult a physician
- Apply liberally to affected area not more than 3 to 4 times daily
- Gently massage into the skin until fully absorbed
- Wash hands with soap and water after each application to avoid spreading to the eyes or other sensitive mucous membranes

Inactive ingredients

Water (Aqua), Glycerin, PEG-75 Lanolin, Polysorbate-20, PEG-40 Hydrogenated Castor Oil, Acrylates/C10-30 Alkyl Acrylate Crosspolymer, Triethanolamine, Emu Oil, Aloe Barbadensis Leaf Juice, Glucosamine HCl, Dimethyl Sulfone, Seed of Celosia Argentea Extract, Ginkgo Biloba Extract, Panax Ginseng Root Extract, Medicago Sativa (Alfalfa) Extract, Cymbopogon Schoenanthus Extract, Tocopheryl Acetate, DMDM Hydantoin, Propylene Glycol, Methylparaben, Propylparaben.

Manufactured by Concept Laboratories, Inc.
Chicago, IL 60642 www.conceptlabs.org

PRINCIPAL DISPLAY PANEL - 244g Bottle Label

NDC 64058-213-18

Immediate
Warming Relief
for Arthritis Joint &
Muscle Pain

FAST™
ARTHRITIS
AID

PAIN
RELIEVING
GEL

NET WT 8.6 OZ. (244g)